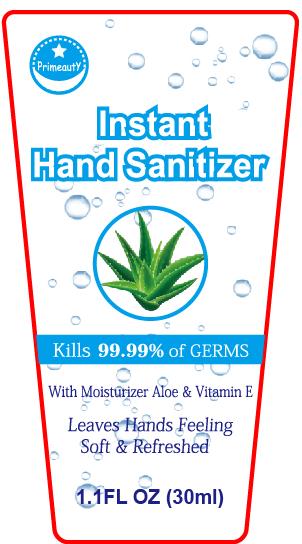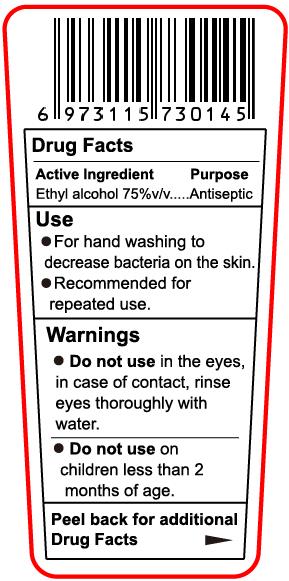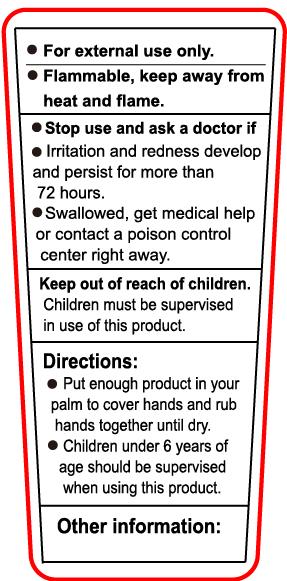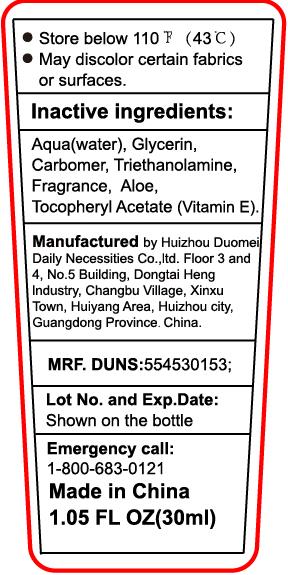 DRUG LABEL: Primeauty Instant Hand Sanitizer
NDC: 75186-007 | Form: GEL
Manufacturer: Huizhou Duomei Daily Necessites Co.,Ltd
Category: otc | Type: HUMAN OTC DRUG LABEL
Date: 20200828

ACTIVE INGREDIENTS: ALCOHOL 75 mL/100 mL
INACTIVE INGREDIENTS: GLYCERIN; TROLAMINE; CARBOMER HOMOPOLYMER, UNSPECIFIED TYPE; WATER; ALOE; .ALPHA.-TOCOPHEROL ACETATE

Active ingredient

Ethyl alcohol 75% v/v

Purpose

Antiseptic

Use

- For hand washing to decrease bacteria on the skin.
- Recommended for repeated use.

Warnings

For external use only.

Flammable, keep away from heat and flame.

Do not use in the eyes, in case of contact, rinse eyes thoroughly with water.

Do not use on children less than 2 months of age.

Stop use and ask a doctor if

- Irritation and redness develop and persist for more than 72 hours.
- Swallowed, get medical help or contact a posion control center right away.

Keep out of reach of children

Children must be supervised in use of this product.

Directions

- Put enough product in your palm to cover hands and rub hands together until dry.
- Children under 6 years of age should be supervised when using this product.

Other information

- Store below 110F （43C）
- May discolor certian fabrics or surfaces.

Inactive ingredients

Aqua(Water),

Glycerin,

Carbomer,

Triethanolamine,

Fragrance,

Aloe,

Tocopheryl Acetate (Vitamin E)